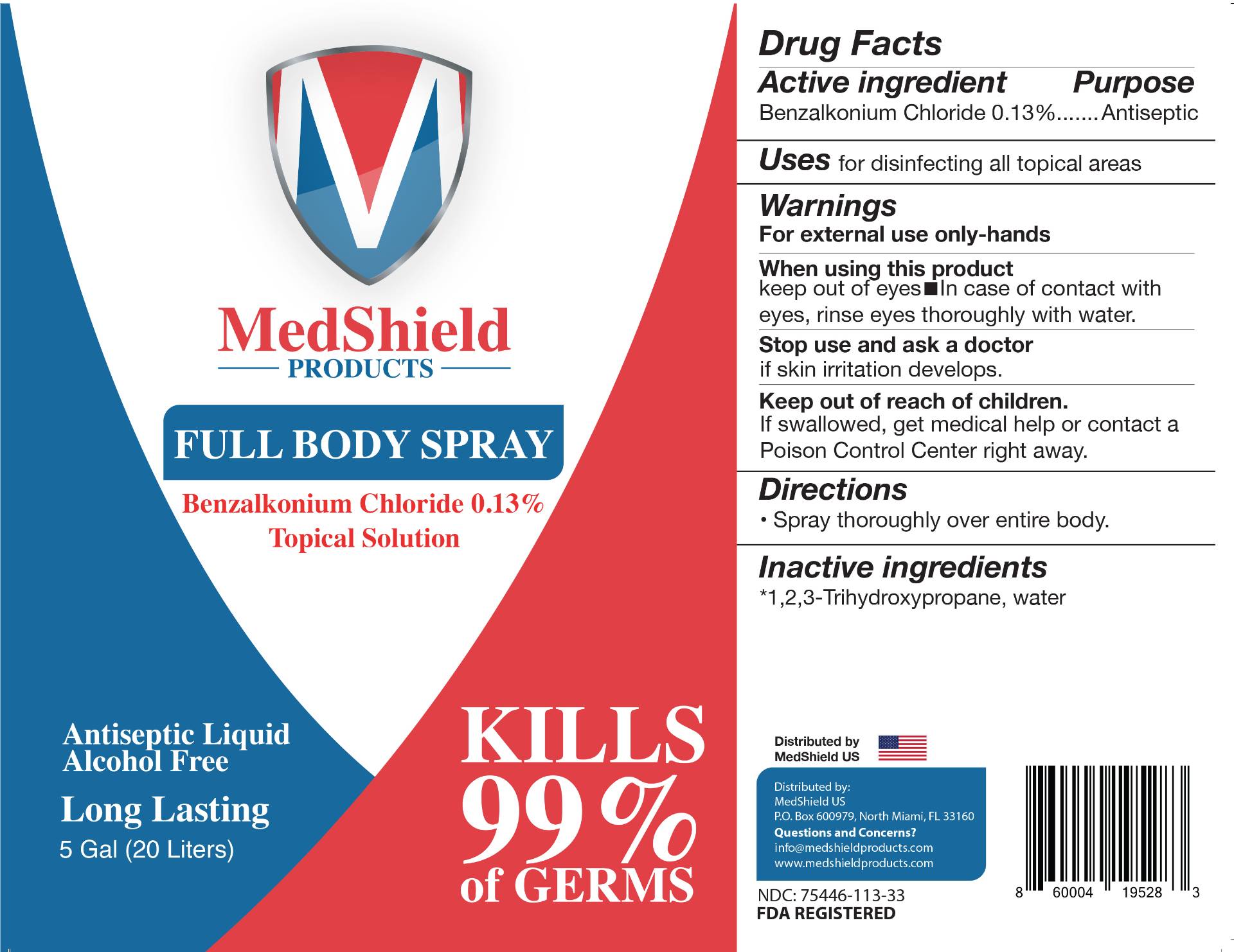 DRUG LABEL: MedShield Products
NDC: 75446-113 | Form: LIQUID
Manufacturer: HWL Holdings, LLC
Category: otc | Type: HUMAN OTC DRUG LABEL
Date: 20200822

ACTIVE INGREDIENTS: BENZALKONIUM CHLORIDE 1.3 ug/1 mL
INACTIVE INGREDIENTS: GLYCERIN; WATER

MedShield 5-Gallon Liquid Spray

Active Ingredient(s)

Benzalkonium Chloride 0.13% Purpose: Antiseptic

Purpose

Antiseptic, Hand Sanitizer

Use

For disinfecting all topical areas.

Warnings

For external use only-hands

WHEN USING

keep out of eyes In case of contact with eyes, rinse eyes thoroughly with water.

STOP USE

if skin irritation develops.

Keep out of reach of children. If swallowed, get medical help or contact a Poison Control Center right away.

Directions

Spray thoroughly over entire body.

Inactive ingredients

*1,2,3-Trihydroxypropane, water

Package Label - Principal Display Panel

20000 mL NDC: 75446-113-33